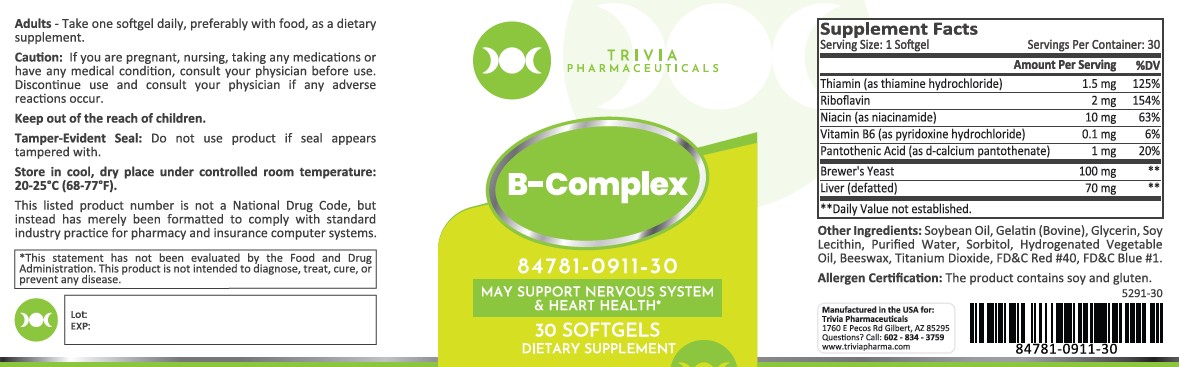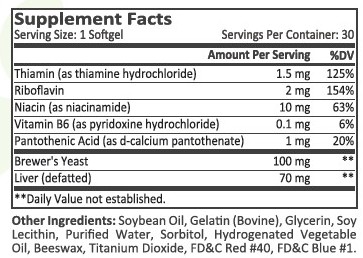 DRUG LABEL: B Complex
NDC: 84781-911 | Form: CAPSULE, GELATIN COATED
Manufacturer: Trivia Pharmaceuticals, LLC
Category: other | Type: Dietary Supplement
Date: 20250922

ACTIVE INGREDIENTS: THIAMINE HCL 1.5 mg/1 1; RIBOFLAVIN 2 mg/1 1; NIACINAMIDE 10 mg/1 1; PANTOTHENIC ACID 1 mg/1 1; PYRIDOXINE HYDROCHLORIDE 0.1 mg/1 1; SACCHAROMYCES CEREVISIAE 100 mg/1 1; BEEF LIVER 70 mg/1 1

B Complex

HEALTH CLAIM:

B Complex Softgels

DESCRIPTION:

B Complex Softgels are clear softgels dispensed in plastic bottles of 30 ct.

84781-0911-30

Reserved for Professional Recommendation

B Complex softgels is an orally administered vitamin to provide significant amounts of B Vitamins to supplement the diet, and to help assure that nutritional deficiencies of these vitamins will not develop.

This listed product is not a National Drug Code, but instead has merely been formatted to comply with standard industry practice for pharmacy and insurance computer systems.

These statements have not been evaluated by the Food and Drug Administration. This product is not intended to diagnose, treat, cure or prevent any disease.

All prescriptions using this product shall be pursuant to state statutes as applicable. This is not an Orange Book product. This product may be administered only under a physician’s supervision. There are no implied or explicit claims on therapeutic equivalence.

Manufactured for:

Trivia Pharmaceuticals, LLC

Gilbert, AZ

WARNINGS:

This product is contraindicated in patients with a known hypersensitivity to any of the ingredients.

Use with caution in patients that may have a medical condition, are pregnant, lactating, trying to conceive, under the age of 18, or taking medications.

These statements have not been evaluated by the Food and Drug Administration. This product is not intended to diagnose, treat, cure, or prevent any disease.

DOSAGE AND ADMINISTRATION:

Usual adult dose is 1 softgel by mouth daily once daily, preferably with food, as a dietary supplement.

PRECAUTIONS:

CONTRAINDICATIONS
This product is contraindicated in patients with known hypersensitivity to any of the ingredients.

PRECAUTIONS
This product is contraindicated in patients with a known hypersensitivity to any of the ingredients.

ADVERSE REACTIONS
Allergic sensitizations have been reported following oral administration of folic acid. Consult your physician immediately if adverse side effects occur.

KEEP OUT OF THE REACH OF CHILDREN.

STORAGE:

Store at 20° to 25°C (68° to 77°F); excursions permitted to 15° to 30°C (59° to 86°F). [See USP Controlled Room Temperature.] Protect from light and moisture.